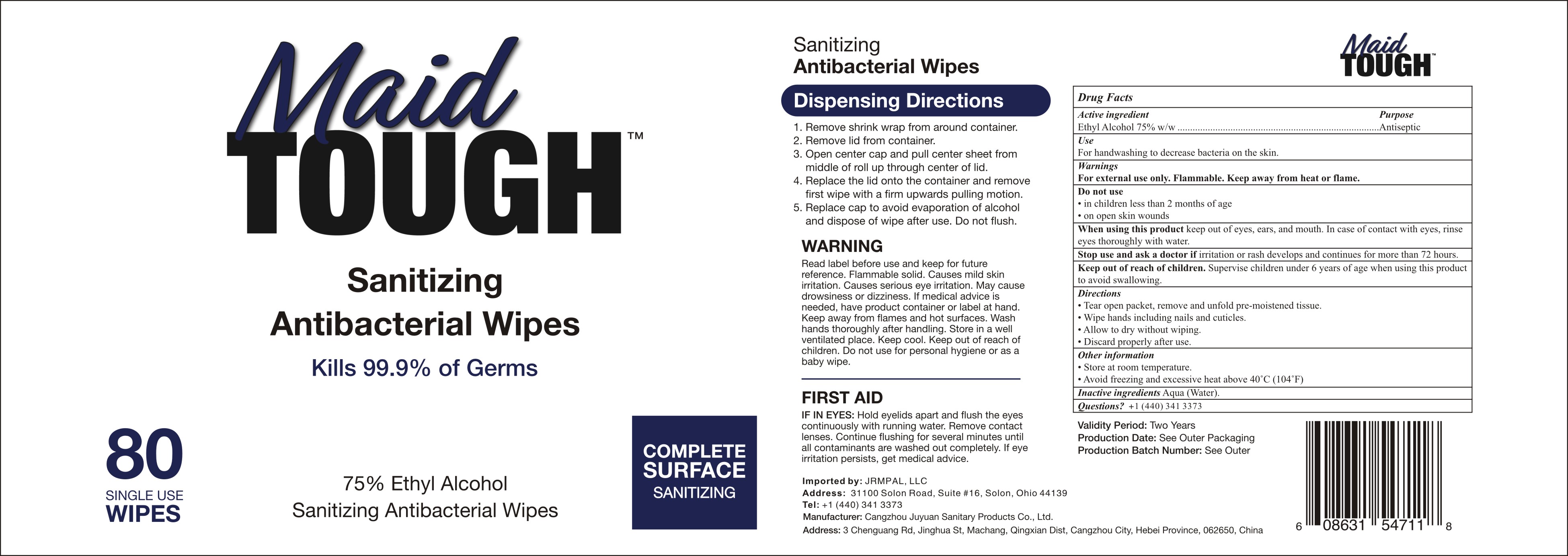 DRUG LABEL: Sanitizing Antibacterial Wipes
NDC: 79621-628 | Form: CLOTH
Manufacturer: Tianjin Zejun Int'l Trade Co., Ltd
Category: otc | Type: HUMAN OTC DRUG LABEL
Date: 20200820

ACTIVE INGREDIENTS: ALCOHOL 75 g/100 g
INACTIVE INGREDIENTS: WATER 25 g/100 g

Active Ingredient(s)

Ethyl Alcohol 75% v/v, Antiseptic

Purpose

Antiseptic, Hand Sanitizer

Use

For handwashing to decrease bacteria on the skin.

Warnings

For external use only. Flammable. Keep away from heat or flame.

Do not use

- in children less than 2 months of age
- on open skin wounds

When using this product keep out of eyes, ears, and mouth. In case of contact with eyes, rinse eyes thoroughly with water.
Stop use and ask a doctor if irritation or rash occurs. These may be signs of a serious condition.
Keep out of reach of children. If swallowed, get medical help or contact a Poison Control Center right away.

Stop use and ask a doctor if irritation or rash develops and continues for more than 72 hours.

Keep out of reach of children. Supervise children under 6 years of age when using this product to avoid swallowing.

Directions

- Tear open packet, remove and unfold pre-moistened tissue.
- Wipe hands including nails and cuticles.
- Allow to dry without wiping.
- Discard properly after use.

Other information

- Store at room temperature.
- Avoid freezing and excessive heat above 40˚C (104˚F)

Inactive ingredients

Aqua(Water).

Package Label - Principal Display Panel

80 Wipes in 1 Pail NDC: 79621-628-01